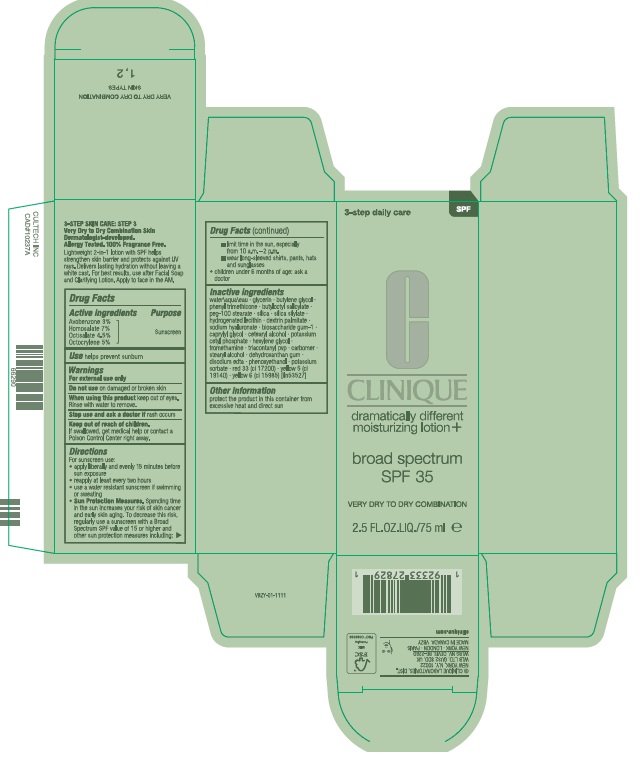 DRUG LABEL: DRAMATICALLY DIFFERENT MOISTURIZING LTN BROAD SPECTRUM SPF35
NDC: 49527-222 | Form: CREAM
Manufacturer: CLINIQUE LABORATORIES LLC
Category: otc | Type: HUMAN OTC DRUG LABEL
Date: 20260115

ACTIVE INGREDIENTS: HOMOSALATE 70 mg/1 mL; OCTISALATE 45 mg/1 mL; AVOBENZONE 30 mg/1 mL; OCTOCRYLENE 50 mg/1 mL
INACTIVE INGREDIENTS: BUTYLENE GLYCOL; POTASSIUM CETYL PHOSPHATE; EDETATE DISODIUM ANHYDROUS; POTASSIUM SORBATE; SODIUM HYALURONATE; FD&C YELLOW NO. 5; PEG-100 STEARATE; SILICA; D&C RED NO. 33; PHENYL TRIMETHICONE; HYDROGENATED SOYBEAN LECITHIN; CETEARYL ALCOHOL; HEXYLENE GLYCOL; TROMETHAMINE; PHENOXYETHANOL; DEXTRIN PALMITATE (CORN; 20000 MW); CARBOMER; WATER; GLYCERIN; BUTYLOCTYL SALICYLATE; BIOSACCHARIDE GUM-1; CAPRYLYL GLYCOL; TRIACONTANYL PVP; STEARYL ALCOHOL; DEHYDROXANTHAN GUM; FD&C YELLOW NO. 6

DRAMATICALLY DIFFERENT MOISTURIZING LOTION+ BROAD SPECTRUM SPF35

Active ingredients

AVOBENZONE 3%

HOMOSALATE 7%

OCTISALATE 4.5%

OCTOCRYLENE 5%

Purpose

Sunscreen

Use

helps prevent sunburn

Warnings

For external use only

Do not use

on damaged or broken skin

When using this product

keep out of eyes. Rinse with water to remove.

Stop use and ask a doctor

if rash occurs

Keep out of reach of children.

If product is swallowed, get medical help or contact a Poison Control Center right away.

Directions

- For sunscreen use:
- apply liberally 15 minutes before sun exposure
- reapply at least every two hours
- use a water resistant sunscreen if swimming or sweating
- Sun Protection Measures. Spending time in the sun increases your risk of skin cancer and early skin aging. To decrease this risk, regularly use a sunscreen with a Broad Spectrum SPF value of 15 or higher and other sun protection measures including:
- limit time in the sun, especially from 10 a.m.–2 p.m.
- wear long-sleeved shirts, pants, hats and sunglasses
- children under 6 months of age: ask a doctor

Inactive Ingredients

water\aqua\eau,glycerin,butylene glycol,phenyl trimethicone,butyloctyl salicylate,peg-100 stearate,silica,silica silylate,hydrogenated lecithin,dextrin palmitate,sodium hyaluronate,biosaccharide gum-1,caprylyl glycol,cetearyl alcohol,potassium cetyl phosphate,hexylene glycol,tromethamine,triacontanyl pvp,carbomer,stearyl alcohol,dehydroxanthan gum,disodium edta,phenoxyethanol,potassium sorbate,red 33 (ci 17200),yellow 5 (ci 19140),yellow 6 (ci 15985) <iln53527>

Other information

protect the product in this container from excessive heat and direct sun

PACKAGE LABEL

CLINIQUE

dramatically different

moisturizing loition +

broad spectrum

SPF35

VERY DRY TO DRY COMBINATION

2.5FL.OZ.LIQ./75 ml